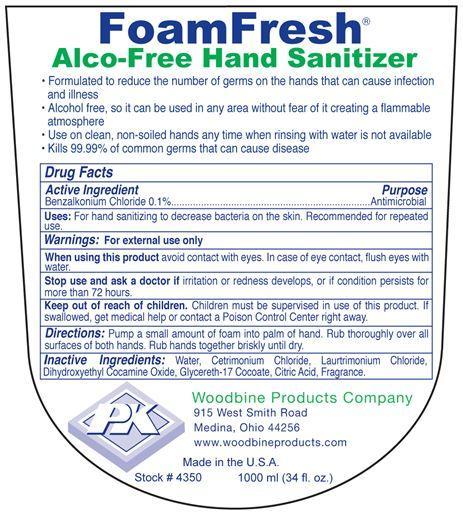 DRUG LABEL: FoamFresh Alco-Free Hand Sanitizer
NDC: 11429-1001 | Form: LIQUID
Manufacturer: Woodbine Products Company
Category: otc | Type: HUMAN OTC DRUG LABEL
Date: 20250617

ACTIVE INGREDIENTS: BENZALKONIUM CHLORIDE 1 mg/1 mL
INACTIVE INGREDIENTS: WATER; CETRIMONIUM CHLORIDE; LAURTRIMONIUM CHLORIDE; DIHYDROXYETHYL COCAMINE OXIDE; GLYCERETH-17 COCOATE; CITRIC ACID MONOHYDRATE

Drug Facts 11429-1001

Active Ingredient

Benzalkonium Chloride 0.1%

Purpose

Antimicrobial

Uses:

For hand sanitizing to decrease bacteria on the skin.

Recommended for repeated use.

Warnings:

For external use only

When using this product avoid contact with eyes.

In case of eye contact, flush eyes with water.

Stop use and ask a doctor if irritation or redness develops, or if conditions persists for more than 72 hours.

Keep out of reach of children.

Children must be supervised in use of this product.

If swallowed, get medical help or contact a Poison Control Center right away.

Directions:

Pump a small amount of foam into palm of hand.

Rub thoroughly over all surfaces of both hands.

Rub hands together briskly until dry.

Inactive Ingredients:

Water, Cetrimonium Chloride, Laurtrimonium Chloride, Dihydroxyethyl Cocamine Oxide, Glycereth-17 Cocoate, Citric Acid, Fragrance.

PACKAGE LABEL

FoamFresh

Alco-Free Hand Sanitizer

Formulated to reduce the number of germs on the hands that can cause infection and illness

Alcohol free, so it can be used in any area without fear of it creating a flammable atmosphere

Use on clean, non-soiled hands any time when rinsing with water is not available

Kills 99.99% of common germs that can cause disease

PK

Woodbine Products Company

915 West Smith Road

Medina, Ohio 44256

wwww.woodbineproducts.com

Made in the U.S.A.

Stock # 4350 1000 ml (34 fl. oz.)